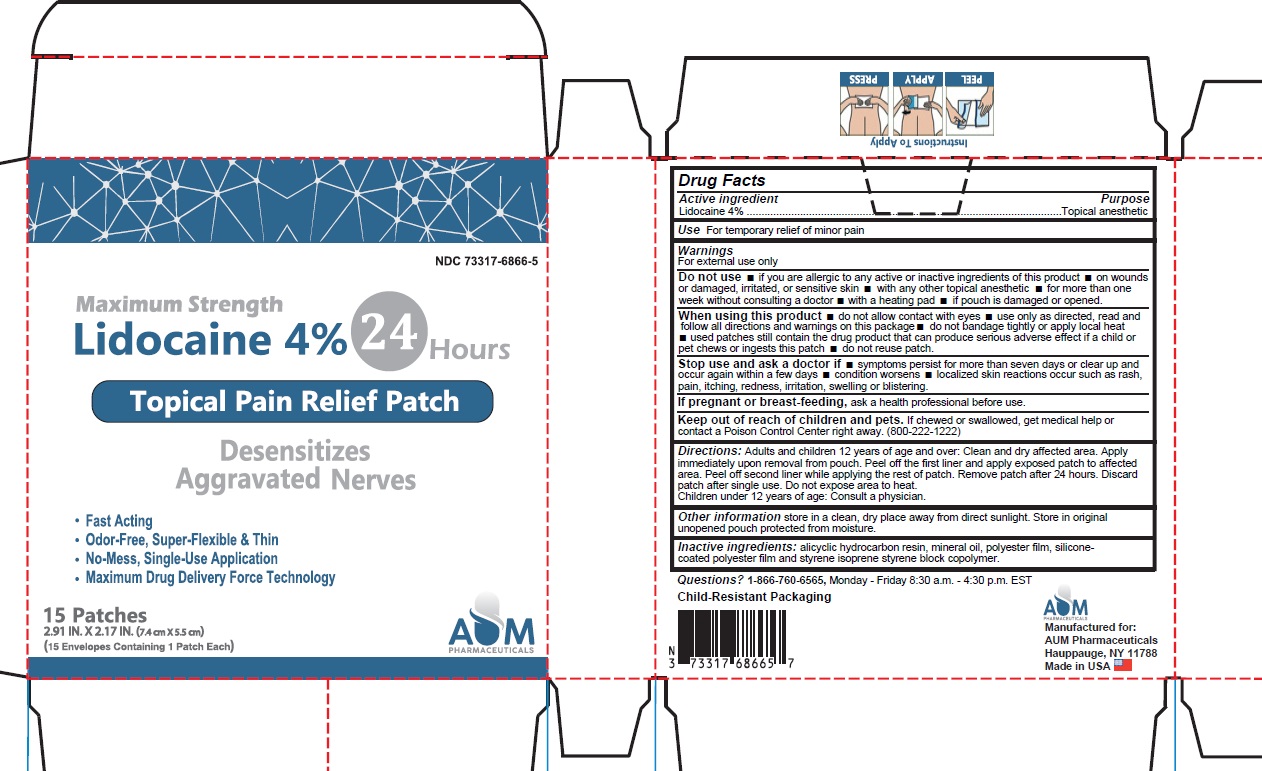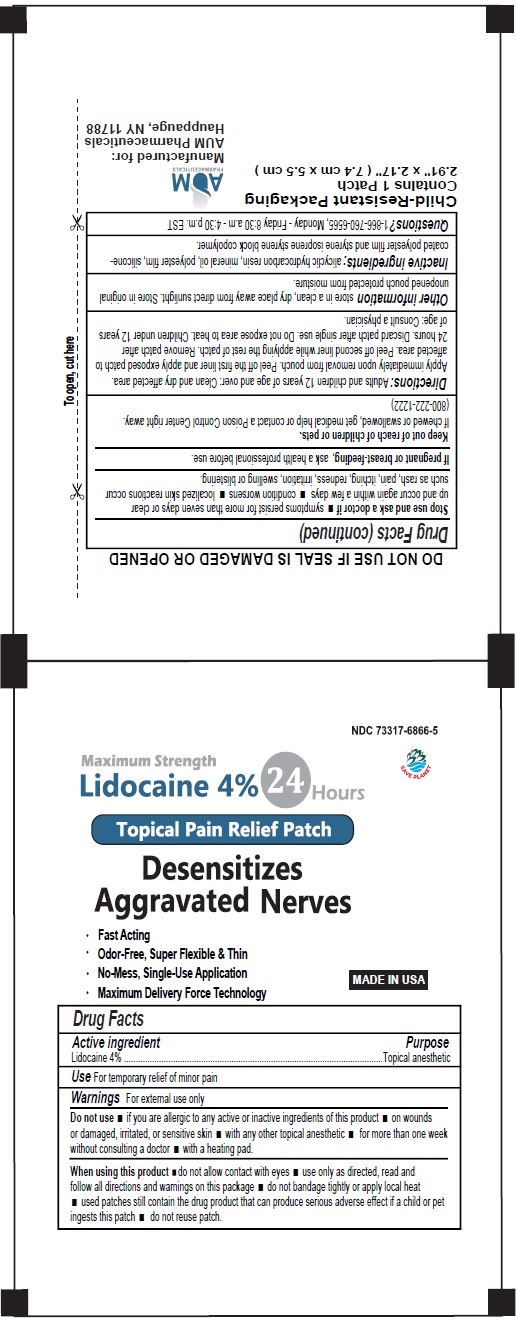 DRUG LABEL: Lidocaine Patch
NDC: 73317-6866 | Form: PATCH
Manufacturer: SLV PHARMACEUTICALS LLC DBA AUM PHARMACEUTICALS
Category: otc | Type: HUMAN OTC DRUG LABEL
Date: 20250820

ACTIVE INGREDIENTS: LIDOCAINE 4 g/100 g
INACTIVE INGREDIENTS: STYRENE/ISOPRENE/STYRENE BLOCK COPOLYMER (STYRENE/ISOPRENE 15/85); HYDROGENATED C6-20 POLYOLEFIN (100 CST); MINERAL OIL

Lidocaine Patch 24 Hours

Active Ingredients

Lidocaine 4% . . . . . . . . . . . . . . . . . . . . . . . . . . . . . . Topical Anesthetic

Purpose

Temporarily relieves minor pain.

Dosage and Administration

Directions Adults and children over 12 years:

■ clean and dry affected area

■ carefully remove backing from patch starting at corner

■ apply sticky side of patch to affected area

■ use one patch for up to 24 hours. Discard patch after single use. Children under 12 years of age: consult a physician.

Warnings

For external use only.

Idications and Usage

Uses: Temporaily relieves minor pains.

When using this product

■ use only as directed

■ read and follow all directions and warnings on this carton

■ do not allow contact with the eyes

■ do not use at the same time as other topical analgesics

■ do not bandage tightly or apply local heat (such as heating pads) to the area of use

■ do not microwave

■ dispose of used patch in manner that always keeps product away from children and pets. Used patches still contain the drug product that can produce serious adverse effects if a child or pet chews or ingests this patch.

Stop use and consult a doctor

■ condition worsens

■ redness is present

■ irritation develops

■ symptoms persist for more than 7 days or clear up and occur again within a few days

■ you experience signs of skin injury, such as pain, swelling or blistering where the product was applied.

PREGNANCY OR BREAST FEEDING

If pregnant or breastfeeding, ask a health professional before use.

Do not Use

■ more than one patch on your body at a time

■ on cut, irritated or swollen skin

■ on puncture wounds

■ for more than one week without consulting a doctor

■ if you are allergic to any active or inactive ingredients

■ if pouch is damaged or opened.

Keep out of reach of children and pets.

If swallowed, get medical help or contact a Poison Control Center right away 800-222-1222

Other Safety Information

Store in a clean, dry place outside of direct sunlight. Protect from excessive moisture.

Inactive Ingredients

Styrene Isoprene Styrene block Copolymer, Alicyclic Saturated Hydrocarbon Resin, White Mineral Oil

Questions

Questions? 1-866-760-6565, Monday - Friday 8:30 a.m - 4:30 p.m. EST

Manufactured for:
AUM Pharmaceuticals
Hauppauge, NY 11788

Made in USA